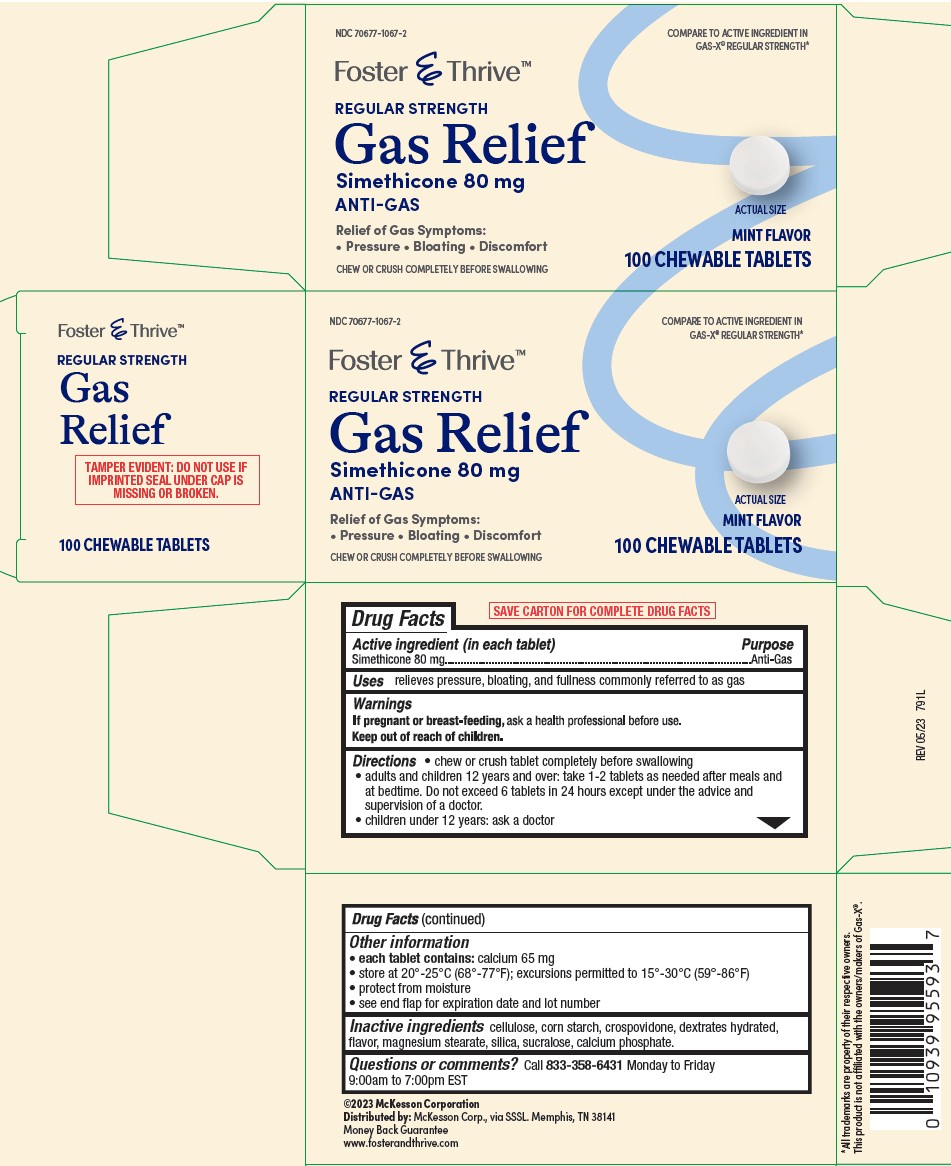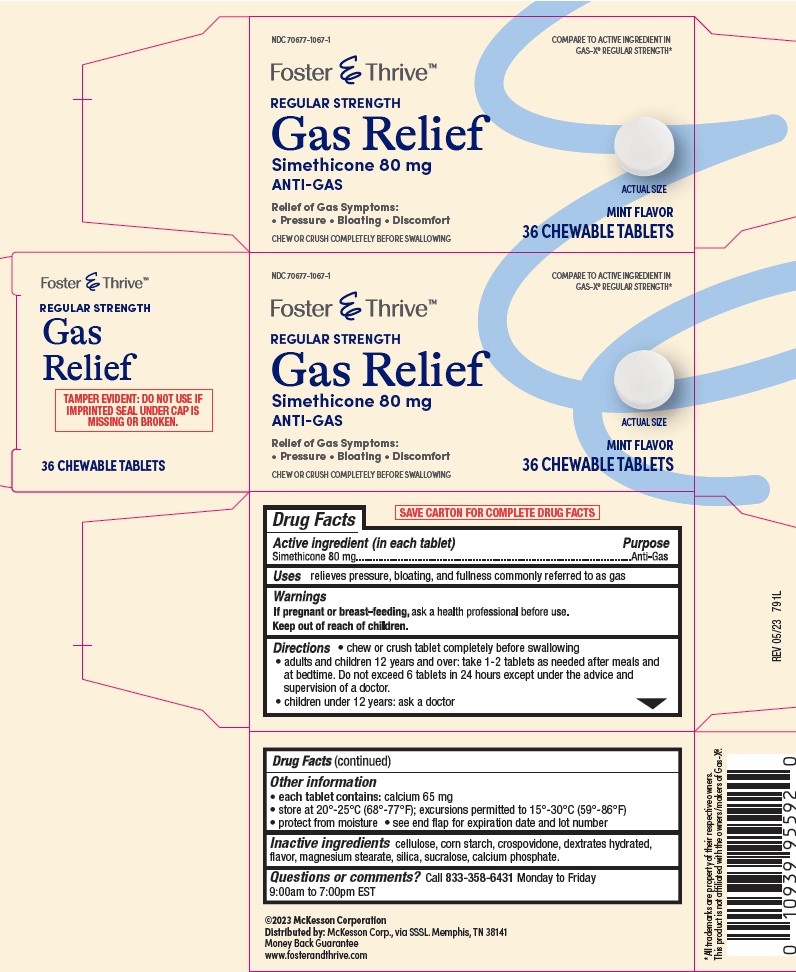 DRUG LABEL: GAS RELIEF
NDC: 70677-1067 | Form: TABLET, CHEWABLE
Manufacturer: STRATEGIC SOURCING SERVICES LLC
Category: otc | Type: HUMAN OTC DRUG LABEL
Date: 20231026

ACTIVE INGREDIENTS: DIMETHICONE 80 mg/1 1
INACTIVE INGREDIENTS: DEXTRATES; SILICON DIOXIDE; TRICALCIUM PHOSPHATE; SUCRALOSE; STARCH, CORN; CROSPOVIDONE; MAGNESIUM STEARATE; CELLULOSE, MICROCRYSTALLINE

FOS 791

Active ingredient (in each tablet)

Simethicone 80 mg

Purpose

Anti-Gas

Uses

relieves pressure, bloating, and fullness
commonly referred to as gas

Warnings

If pregnant or breast feeding, ask a health professional before use.

Keep out of reach of children.

Directions

- chew or crush tablet completely before swallowing
- adults and children 12 years and over: take 1-2 tablets as needed after meals and at bedtime.

Do not exceed 6 tablets in 24 hours except under the advice and supervision of a doctor.

- children under 12 years: ask a doctor

Other information

- each tablet contains: calcium 65 mg
- store at 20°-25°C (68°-77°F); excursions permitted to 15°-30°C (59°-86°F)
- protect from moisture
- see end flap for expiration date and lot number

Inactive ingredients

cellulose, corn starch, crospovidone, dextrates hydrated, flavor,
magnesium stearate, silica, sucralose, calcium phosphate.

Questions or comments?

Call 833-358-6431 Monday to Friday 9:00am to 7:00pm EST